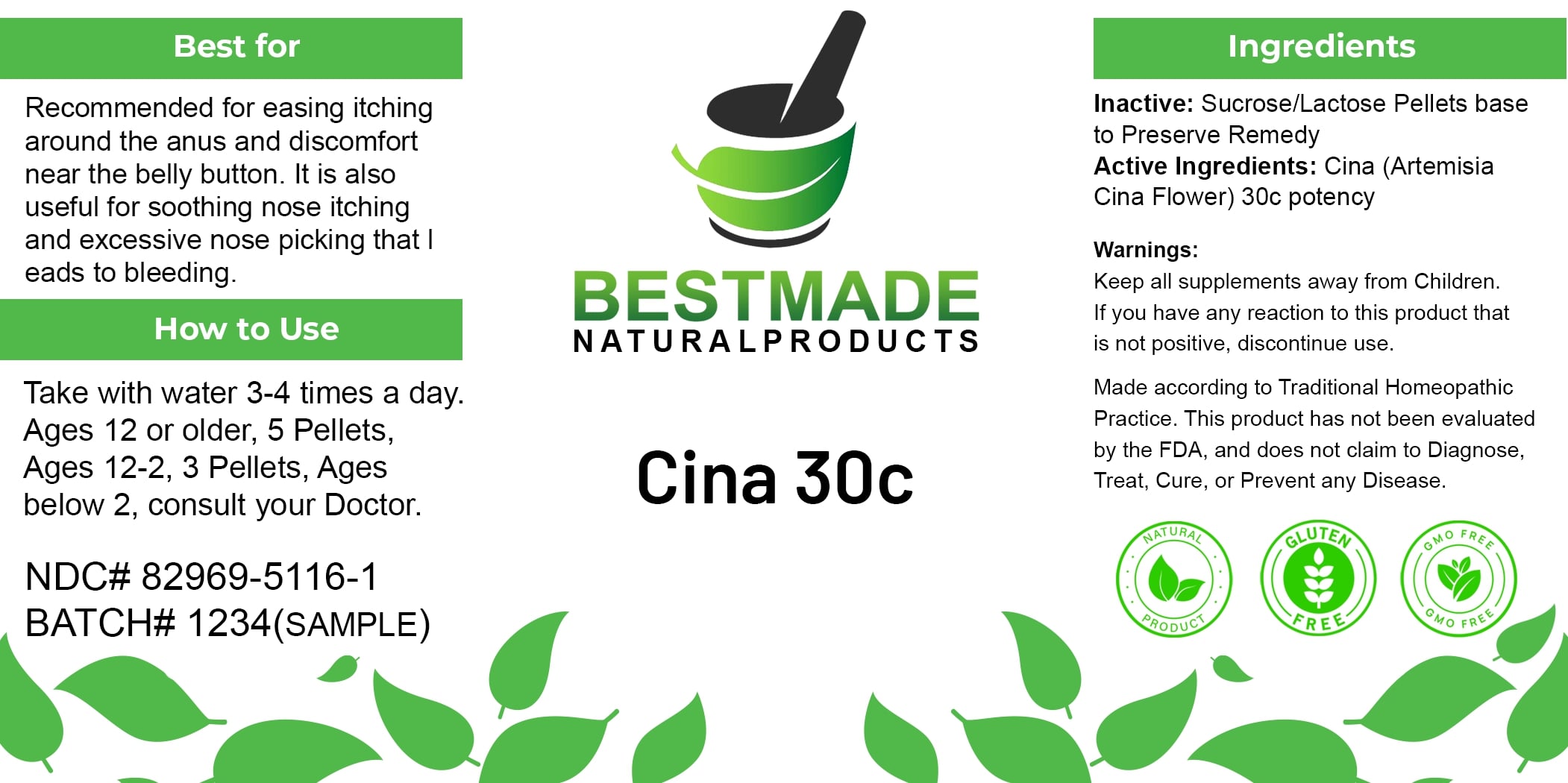 DRUG LABEL: Bestmade Natural Products Cina 30c
NDC: 82969-5116 | Form: TABLET, SOLUBLE
Manufacturer: Bestmade Natural Products
Category: homeopathic | Type: HUMAN OTC DRUG LABEL
Date: 20241223

ACTIVE INGREDIENTS: ARTEMISIA CINA FLOWER 30 [hp_C]/30 [hp_C]
INACTIVE INGREDIENTS: LACTOSE, UNSPECIFIED FORM 30 [hp_C]/30 [hp_C]; SUCROSE 30 [hp_C]/30 [hp_C]

Cina 30c

DOSAGE AND ADMINISTRATION

Take with water 3-4 times a day

Ages 12 or older, 5 Pellets, Ages 12-2, 3 Pellets, Ages below 2, consult your Doctor.

INDICATIONS AND USAGE

Best for

Recommended for easing itching around the anus and discomfort near the belly button. It is also useful for soothing nose itching and excessive nose picking that Ieads to bleeding.

INACTIVE INGREDIENT

Ingredients

Inactive: Sucrose/Lactose Pellets base to Preserve Remedy

Active Ingredients: Cina (Artemisia Cina Flower) 30c potency

Warnings:

Keep all supplements away from Children.

If you have any reaction to this product that is not positive, discontinue use.

Made according to Traditional Homeopathic Practice. This product has not been evaluated by the FDA, and does not claim to Diagnose, Treat, Cure, or Prevent any Disease.

PURPOSE

Best for

Recommended for easing itching around the anus and discomfort near the belly button. It is also useful for soothing nose itching and excessive nose picking that Ieads to bleeding.

Warnings:

Keep all supplements away from Children.

If you have any reaction to this product that is not positive, discontinue use.

Made according to Traditional Homeopathic Practice. This product has not been evaluated by the FDA, and does not claim to Diagnose, Treat, Cure, or Prevent any Disease.

Entire package label